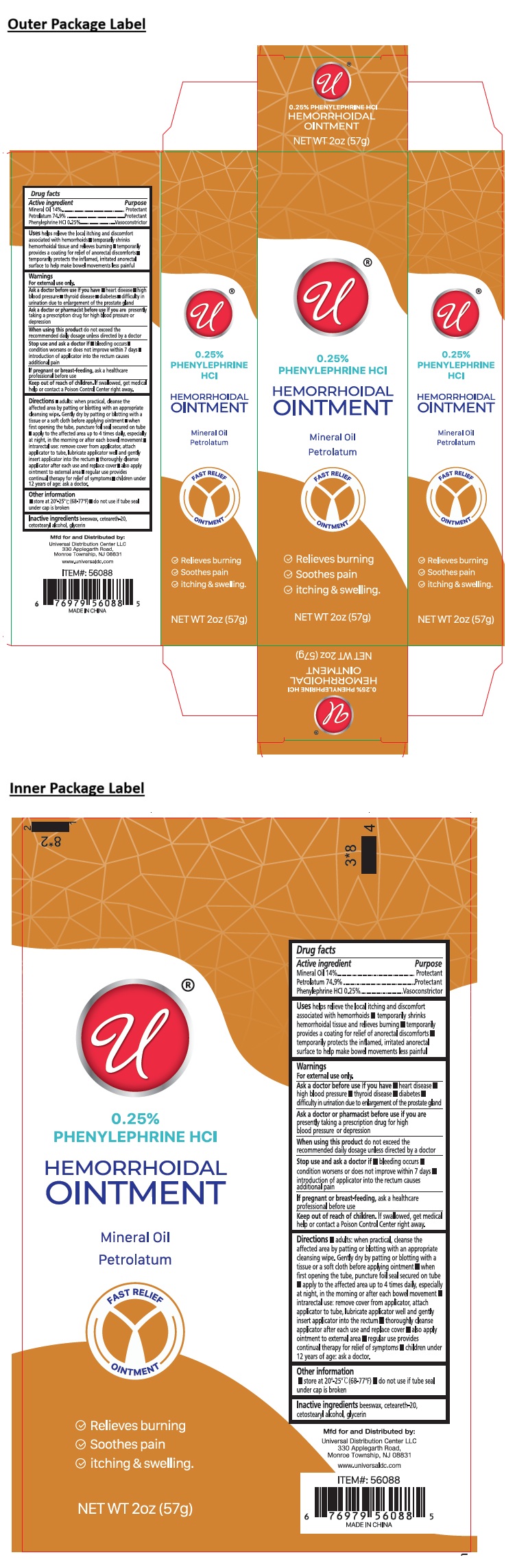 DRUG LABEL: 0.25 % PHENYLEPHRINE HCl HEMORRHOIDAL
NDC: 43473-094 | Form: OINTMENT
Manufacturer: Nantong Health & Beyond Hygienic Products Inc.
Category: otc | Type: HUMAN OTC DRUG LABEL
Date: 20260205

ACTIVE INGREDIENTS: MINERAL OIL 14 g/100 g; PETROLATUM 74.9 g/100 g; PHENYLEPHRINE HYDROCHLORIDE 0.25 g/100 g
INACTIVE INGREDIENTS: YELLOW WAX; POLYOXYL 20 CETOSTEARYL ETHER; CETOSTEARYL ALCOHOL; GLYCERIN

43473-094 0.25 % PHENYLEPHRINE HCl HEMORRHOIDAL OINTMENT

Active ingredient

Mineral Oil 14%
Petrolatum 74.9%
Phenylephrine HCl 0.25%

Purpose

Protectant
Protectant
Vasoconstrictor

Uses

helps relieve the local itching and discomfort associated with hemorrhoids • temporarily shrinks hemorrhoidal tissue and relieves burning • temporarily provides a coating for relief of anorectal discomforts • temporarily protects the inflamed, irritated anorectal surface to help make bowel movements less painful

Warnings

For external use only.

Ask a doctor before use if you have • heart disease • high blood pressure • thyroid disease • diabetes • difficulty in urination due to enlargement of the prostate gland

Ask a doctor or pharmacist before use if you arepresently taking a prescription drug for high blood pressure or depression

When using this productdo not exceed the recommended daily dosage unless directed by a doctor

Stop use and ask a doctor if • bleeding occurs • condition worsens or does not improve within 7 days • introduction of applicator into the rectum causes additional pain

If pregnant or breast-feeding, ask a healthcare professional before use

Keep out of reach of children.If swallowed, get medical help or contact a Poison Control Center right away.

Directions

• adults: when practical, cleanse the affected area by patting or blotting with an appropriate cleansing wipe. Gently dry by patting or blotting with a tissue or a soft cloth before applying ointment • when first opening the tube, puncture foil seal secured on tube • apply to the affected area up to 4 times daily, especially at night, in the morning or after each bowel movement • intrarectal use: remove cover from applicator, attach applicator to tube, lubricate applicator well and gently insert applicator into the rectum • thoroughly cleanse applicator after each use and replace cover • also apply ointment to external area • regular use provides continual therapy for relief of symptoms • children under 12 years of age: ask a doctor.

Other information

• store at 20°–25°C (68°–77°F) • do not use if tube seal under cap is broken

Inactive ingredients

beeswax, ceteareth-20, cetostearyl alcohol, glycerin

FAST RELIEF OINTMENT

✓ Relieves burning
✓ Soothes pain
✓ itching & swelling

Mfd for and Distributed by:
Universal Distribution Center LLC
330 Applegarth Road,
Monroe Township, NJ 08831
www.universaldc.com

MADE IN CHINA